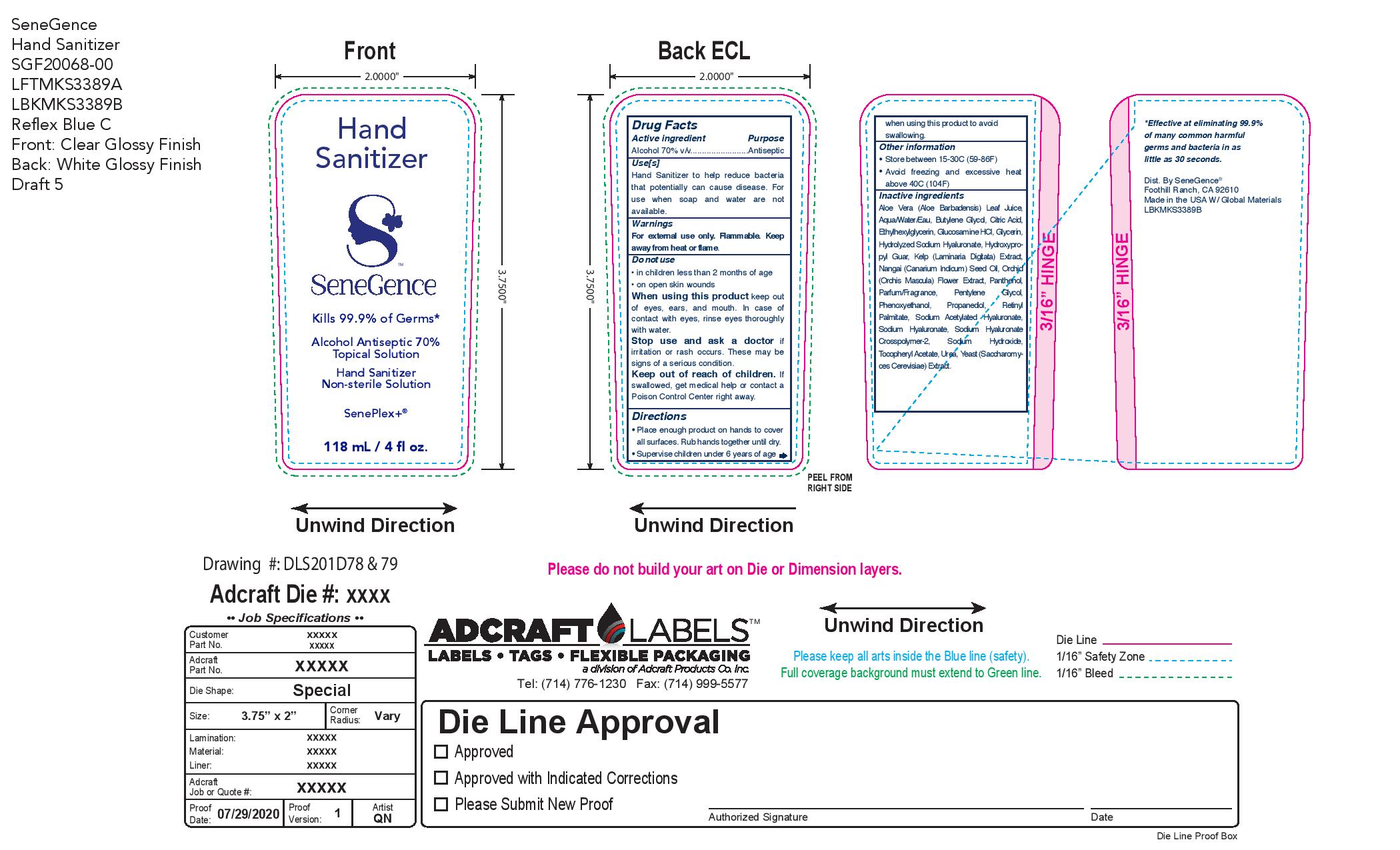 DRUG LABEL: Senegence Hand Sanitizer
NDC: 72644-637 | Form: LIQUID
Manufacturer: SGII, Inc
Category: otc | Type: HUMAN OTC DRUG LABEL
Date: 20210319

ACTIVE INGREDIENTS: ALCOHOL 140 mL/200 mL
INACTIVE INGREDIENTS: ETHYLHEXYLGLYCERIN; FRAGRANCE CLEAN ORC0600327; LIMONENE, (+)-; SODIUM HYDROXIDE; BUTYLENE GLYCOL; UREA; PHENOXYETHANOL; HYALURONATE SODIUM; CANARIUM INDICUM SEED OIL; ALOE VERA LEAF; LAMINARIA DIGITATA; ISOEUGENOL; YEAST; ALPHA-TOCOPHEROL ACETATE; PENTYLENE GLYCOL; HYDROXYCITRONELLAL; BENZYL SALICYLATE; GERANIOL; LINALOOL, (+/-)-; TERT-BUTYL ALCOHOL; PANTHENOL; VITAMIN A PALMITATE; DENATONIUM BENZOATE; GLYCERIN; WATER; GUARAPROLOSE (1300 MPA.S AT 1%); GLUCOSAMINE HYDROCHLORIDE; CITRIC ACID MONOHYDRATE; ORCHIS MASCULA FLOWER

Senegence Hand Sanitizer

Active Ingredients

Alcohol 70% v/v

Purpose

Alcohol 70% v/v.........................Antiseptic

Uses

Hand Sanitizer to help reduce bacteria that potentially can cause disease. For use when soap and water are not available

Warnings

For external use only. Flammable. Keep away from heat or flame.

Do not use
• on children less than 2 months of age
• on open skin wounds

When using this product keep out of eyes, ears, and mouth. In case of contact with eyes, rinse eyes thoroughly with water.

Stop use and ask a doctor if irritation or rash occurs. These may be signs of a serious condition

Keep out of reach of children. If swallowed, get medical help or contact a Poison Control Center right away

Directions

• Place enough product on hands to cover all surfaces. Rub hands together until dry.

• Supervise children under 6 years of age when using this product to avoid swallowing.

Other Information

- Store between 15-30C (59-86F)
- Avoid freezing and excessive heat above 40C (104F)

Inactive Ingredients

Aqua/Water/Eau, Propanediol, Glycerin, Hydroxypropyl Guar, Nangai (Canarium Indicum) Seed Oil, Aloe Vera (Aloe Barbadensis) Leaf Juice, Kelp (Laminaria Digitata) Extract, Yeast (Saccharomyces Cerevisiae) Extract, Orchid (Orchis Mascula) Flower Extract, Sodium Hyaluronate, Sodium Hyaluronate Crosspolymer-2, Hydrolyzed Sodium Hyaluronate, Sodium Acetylated Hyaluronate, Tocopheryl Acetate, Panthenol, Glucosamine HCl, Retinyl Palmitate, Citric Acid, Denatonium Benzoate, T-Butyl Alcohol, Sodium Hydroxide, Alcohol Denat., Butylene Glycol, Urea*, Pentylene Glycol, Phenoxyethanol, Ethylhexylglycerin, Parfum/Fragrance, Hydroxycitronellal, Benzyl Salicylate, Limonene, Geraniol, Linalool, Isoeugenol. *Synthetic